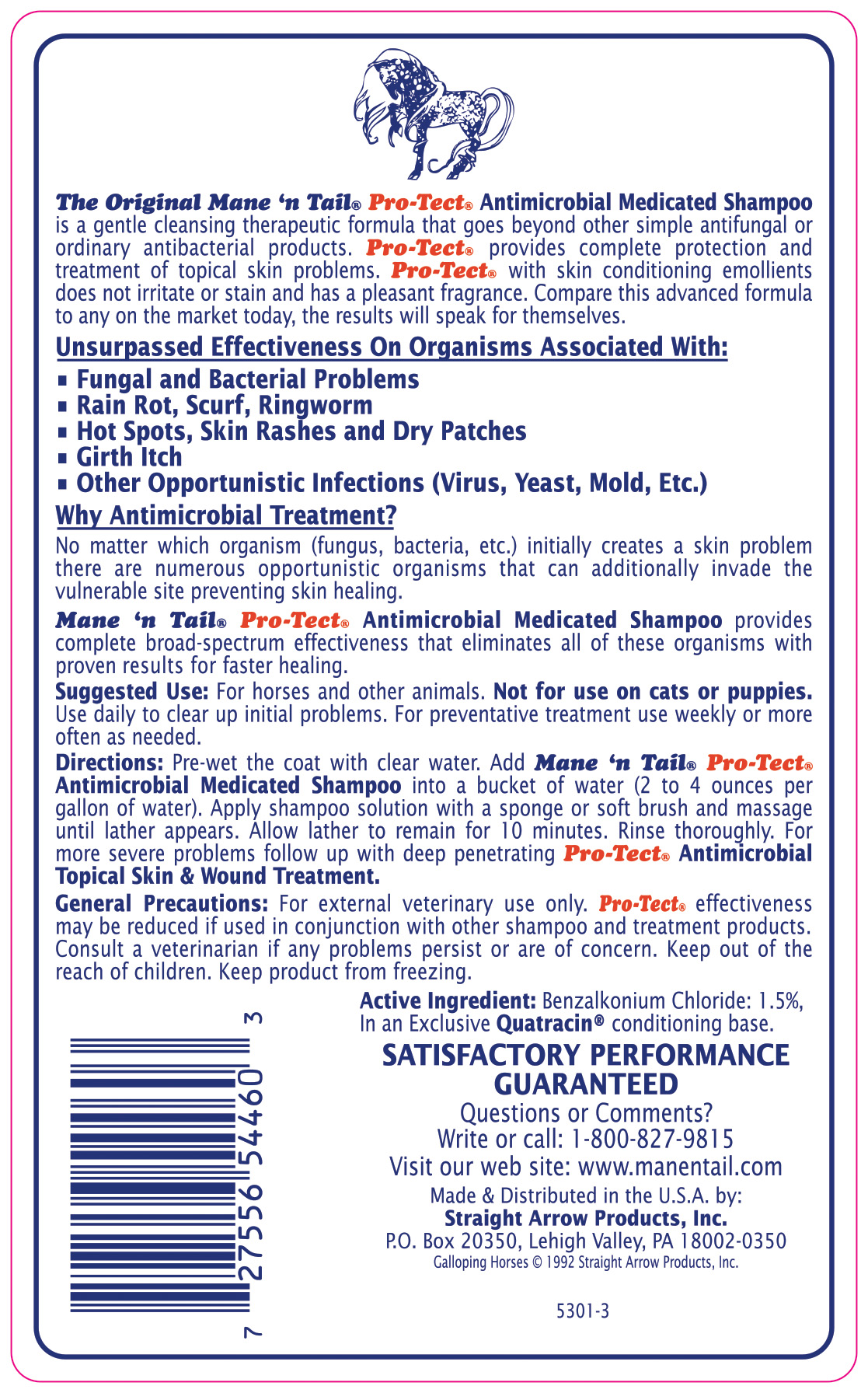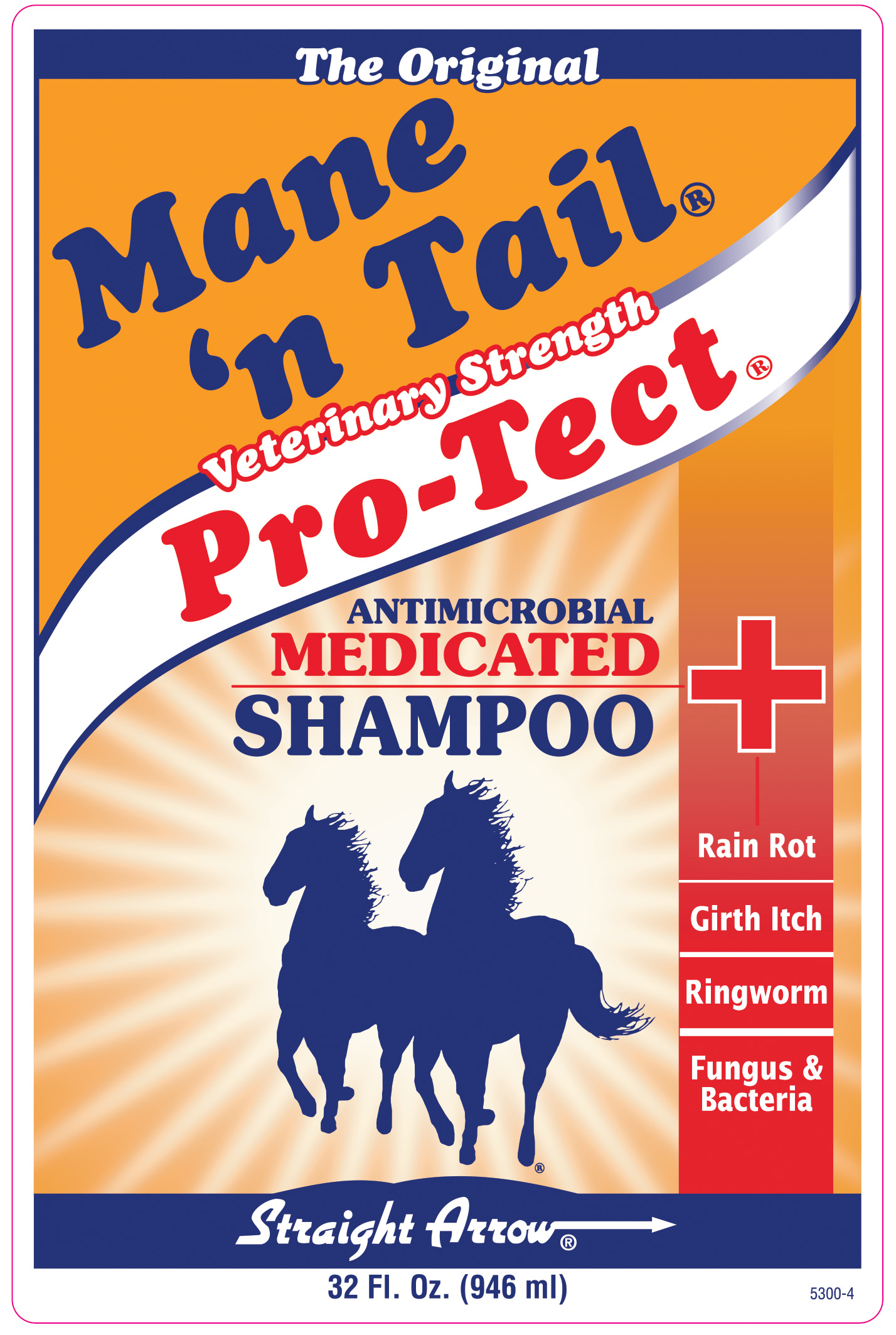 DRUG LABEL: Mane and Tail Veterinary Strength Pro-Tect Antimicrobial Medicated
NDC: 62001-0333 | Form: SHAMPOO
Manufacturer: Straight Arrow Products, Inc.
Category: animal | Type: OTC ANIMAL DRUG LABEL
Date: 20250708

ACTIVE INGREDIENTS: BENZALKONIUM CHLORIDE .015 g/1 g

Mane and Tail Veterinary Strength Pro-Tect Antimicrobial Medicated

Active Ingredient: Benzalkonium Chloride: 1.5% in an exclusive Quatracin conditioning base.

PURPOSE

Mane 'n Tail Pro-Tect Antimicrobial Medicated Shampoo provides complete broad spectrum effectiveness that eliminates all of these organisms with proven results for faster healing.

INDICATIONS AND USAGE

Suggested Use: For horses and other animals. Not for use on cats or puppies. Use daily to clear up initial problems. For preventive treatment use weekly or more often as needed.
Directions: Pre-wet the coat with clear water. Add Mane 'n Tail Pro-Tect Antimicrobial Medicated Shampoo into a bucket of water (2 to 4 ounces per gallon of water). Apply shampoo solution with a sponge or soft brush and massage until lather appears. Allow lather to remain for 10 minutes. Rinse thoroughly. For more severe problems follow up with deep penetrating Pro-Tect Antimicrobial Topical Skin and Wound Treatment.

WARNINGS AND PRECAUTIONS

General Precautions: For external veterinary use only. Pro-Tect effectiveness may be reduced if used in conjunction with other shampoo and treatment products. Consult a veterinarian if any problems persist or are of concern. Keep out of the reach of children. Keep product from freezing.